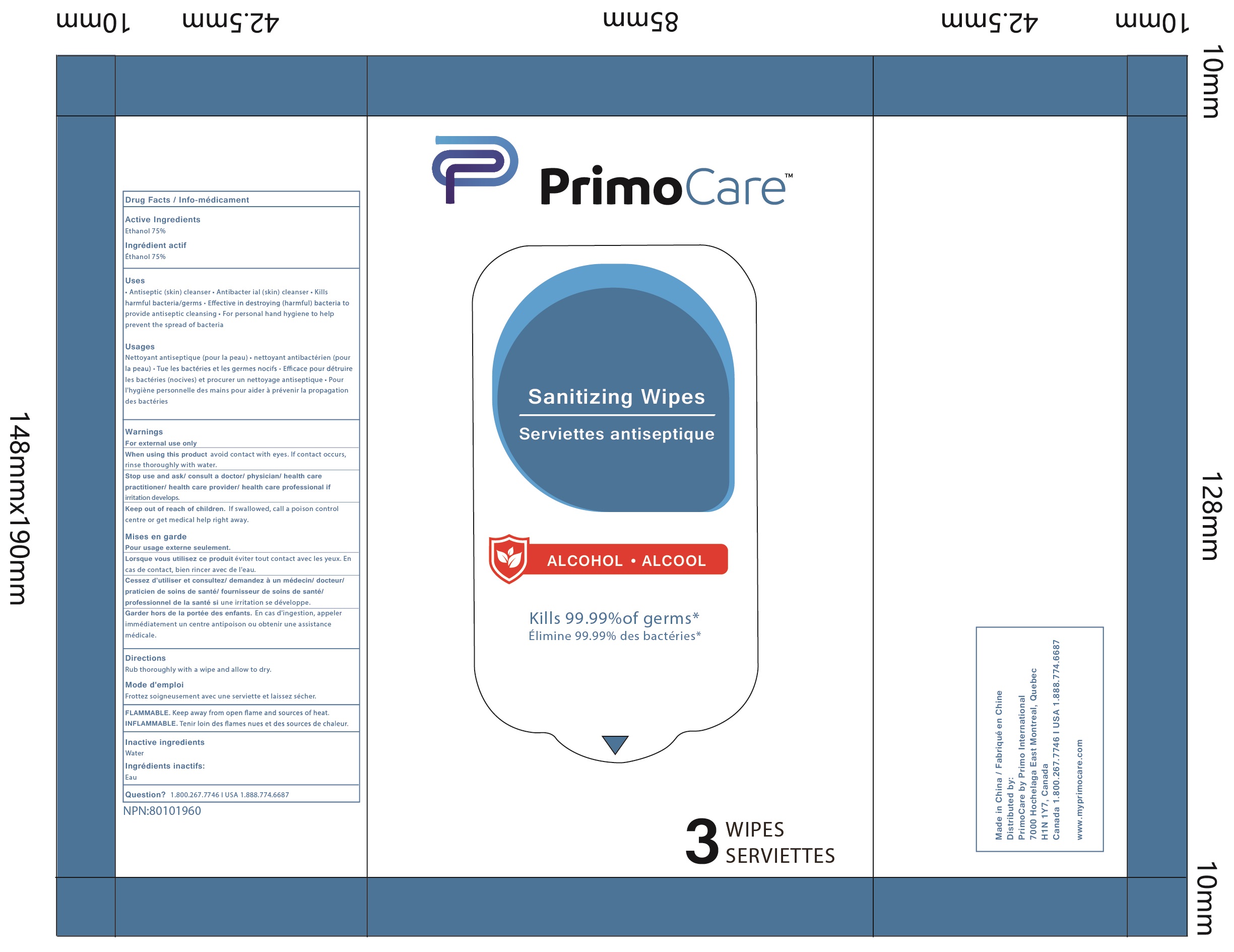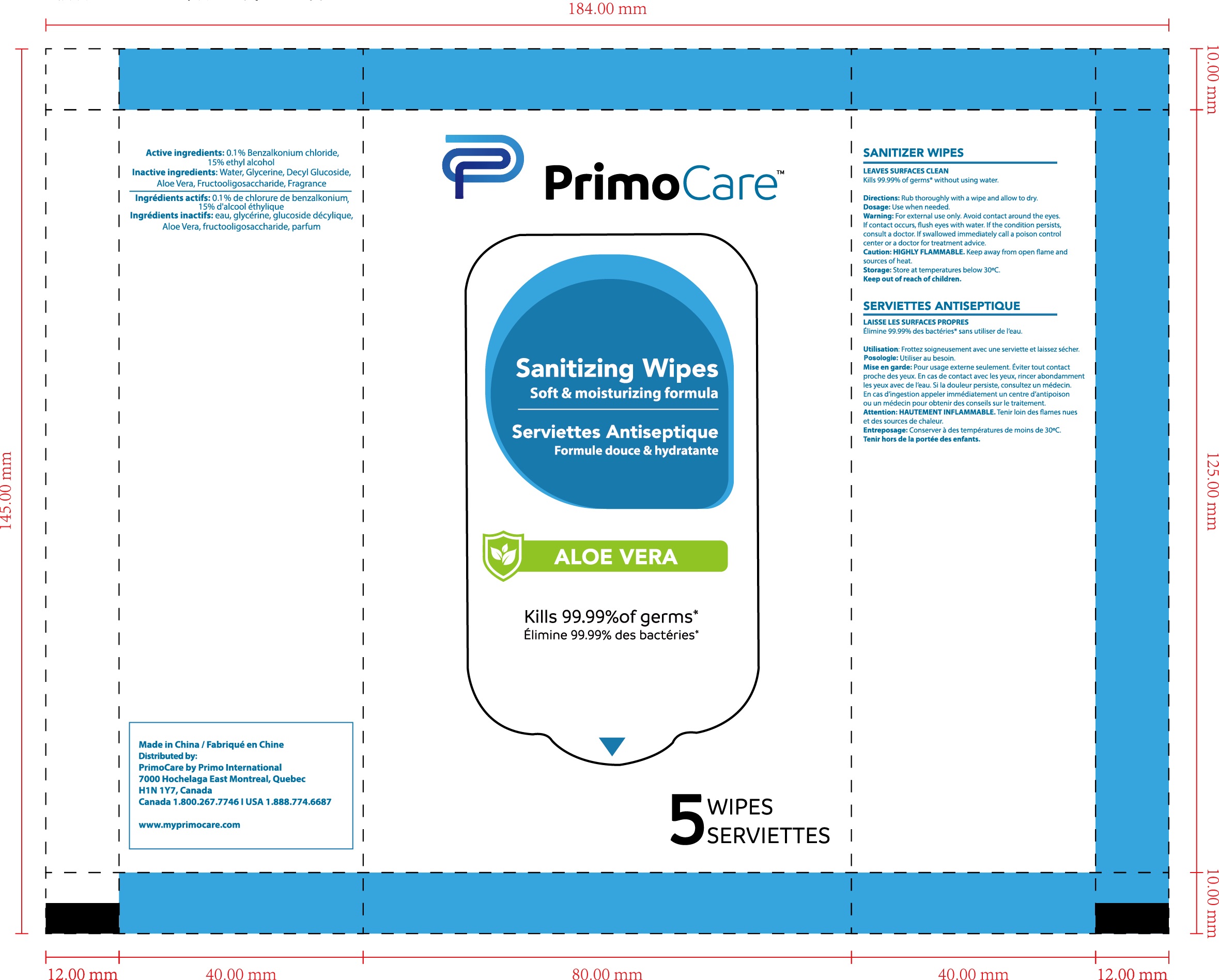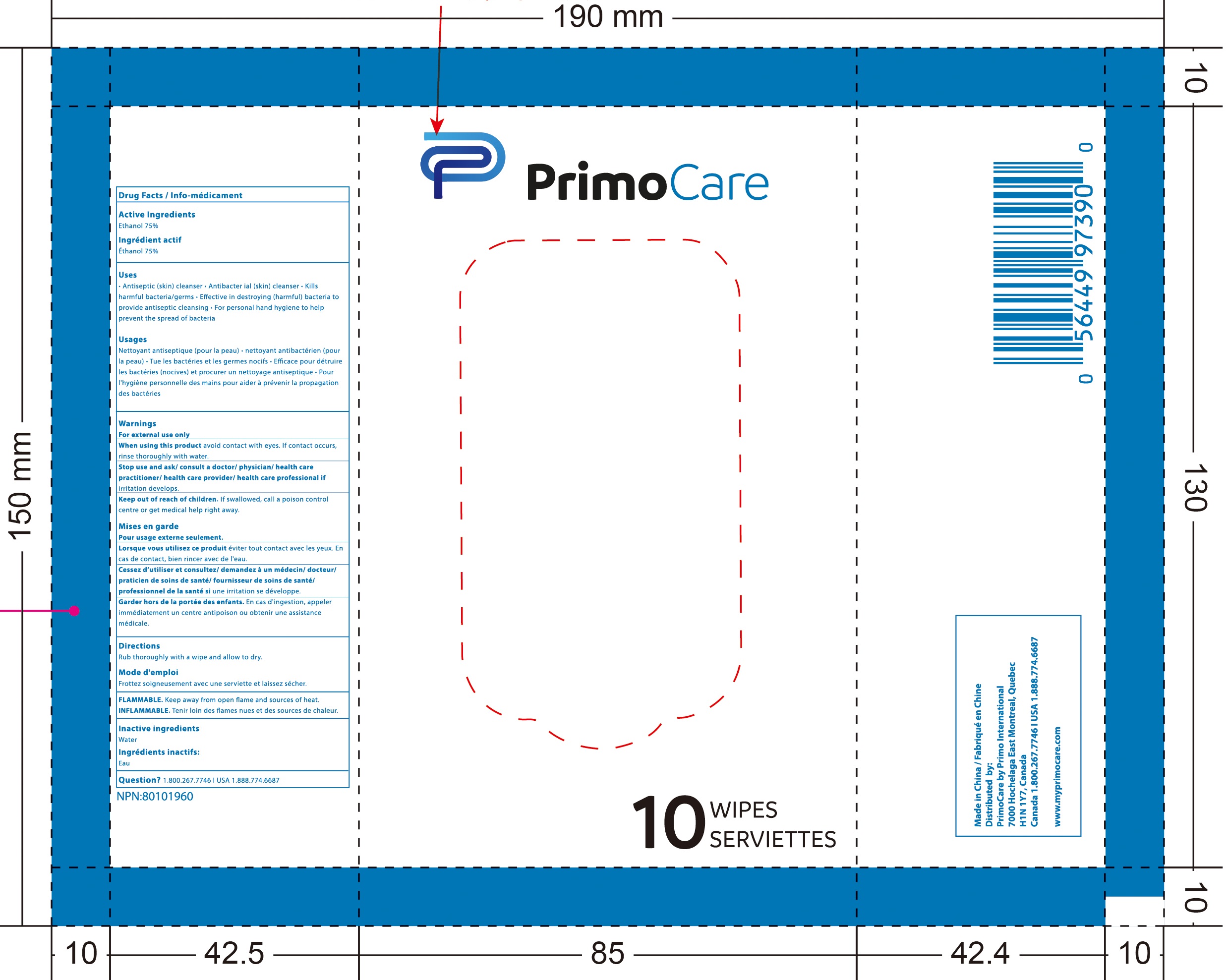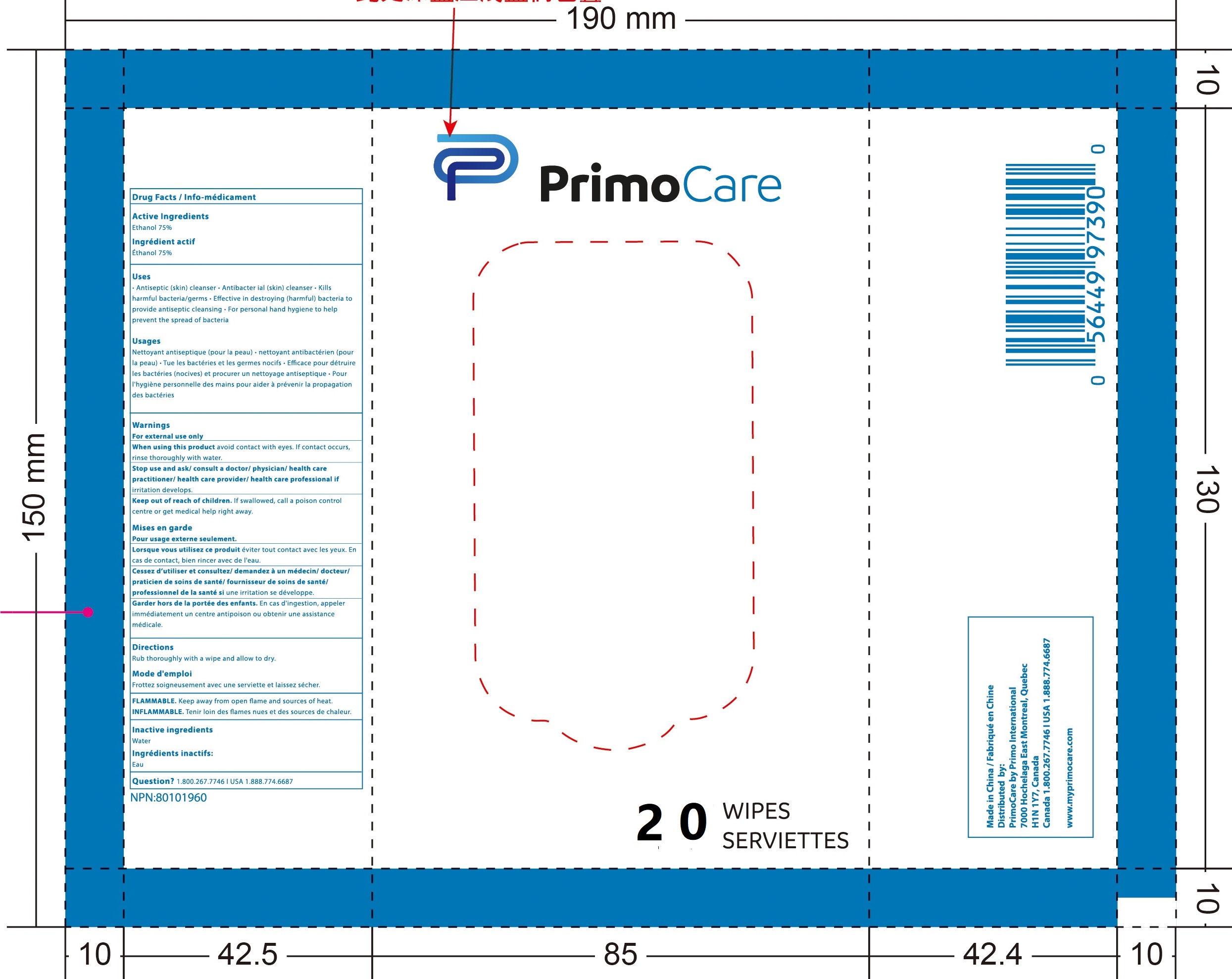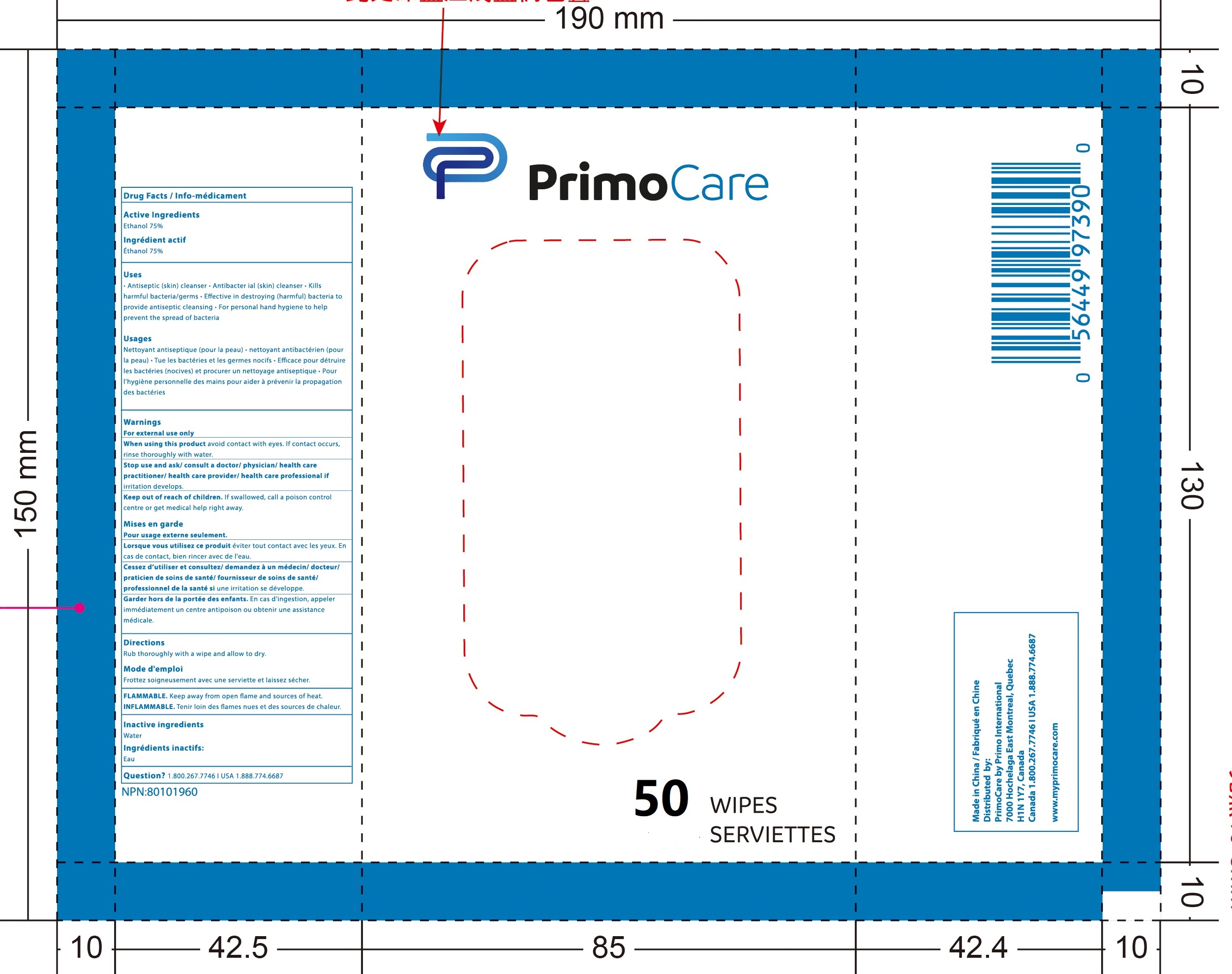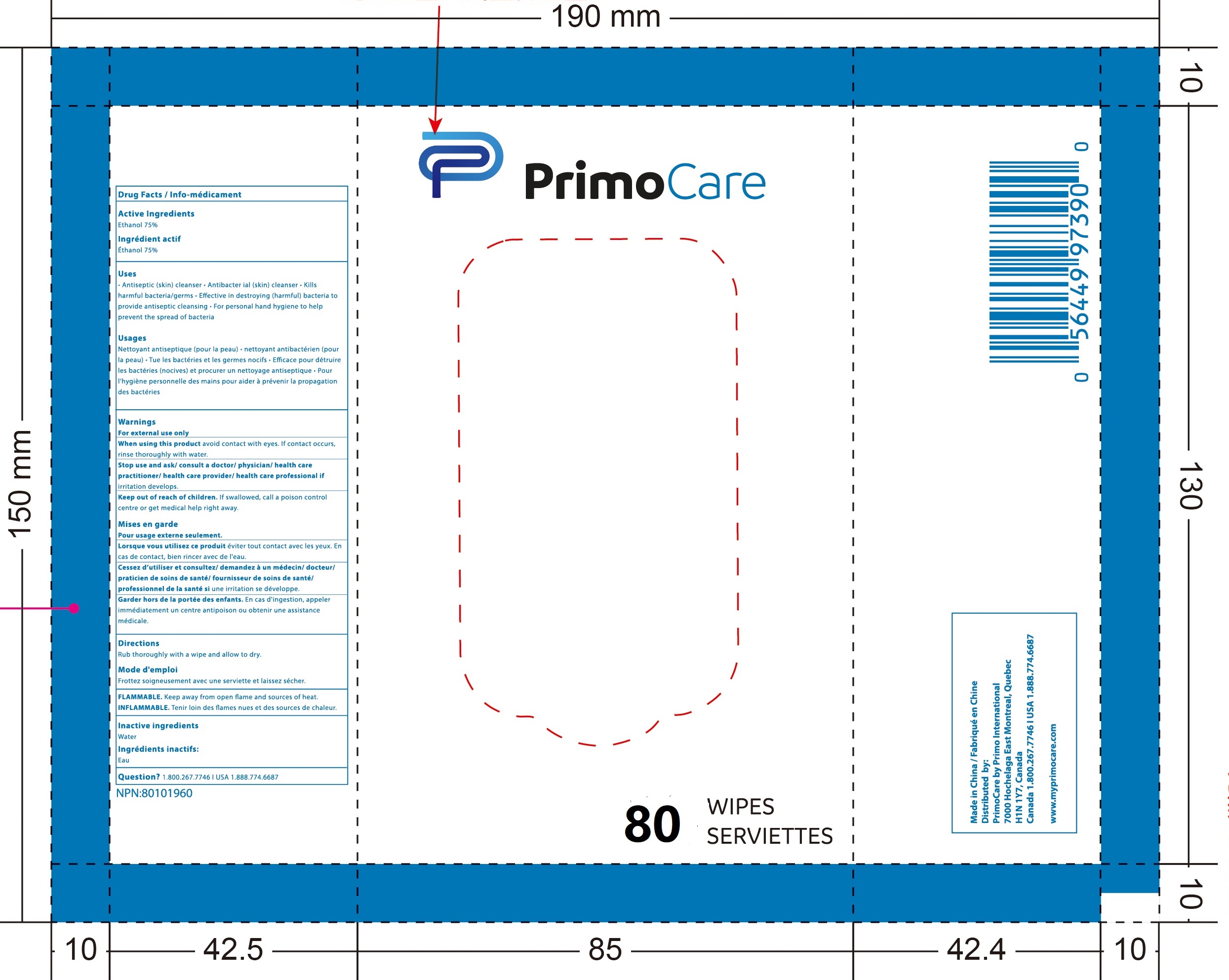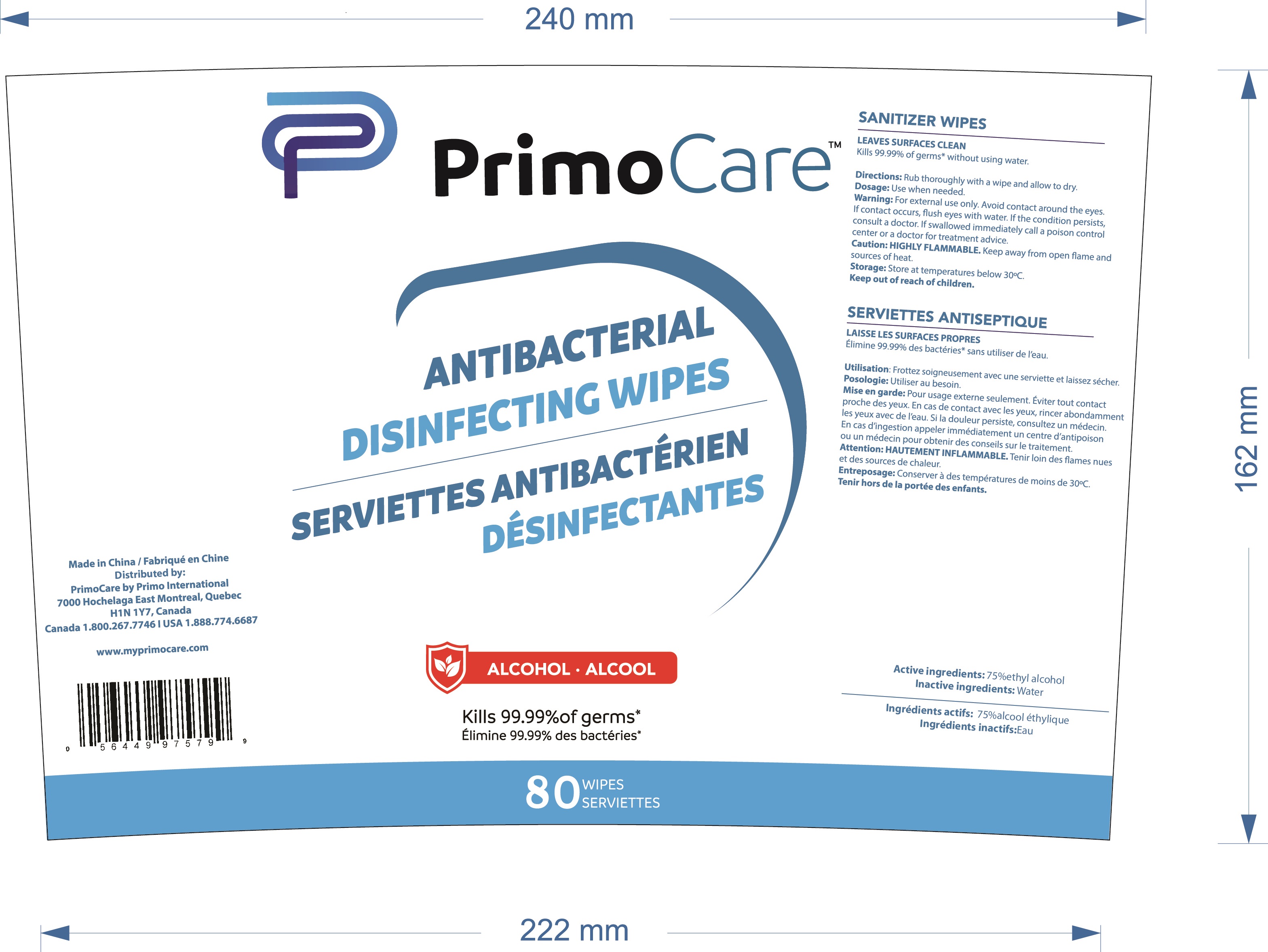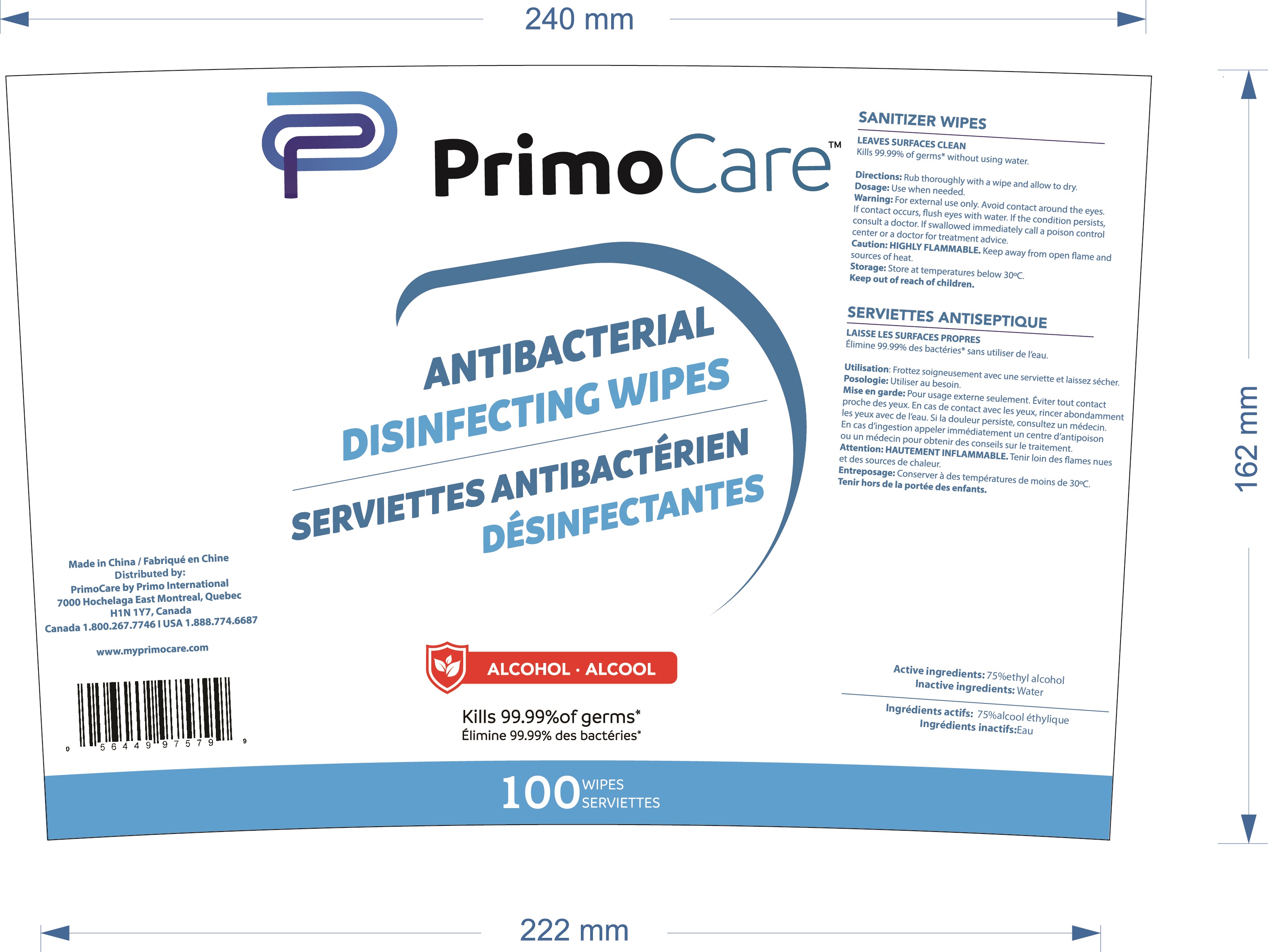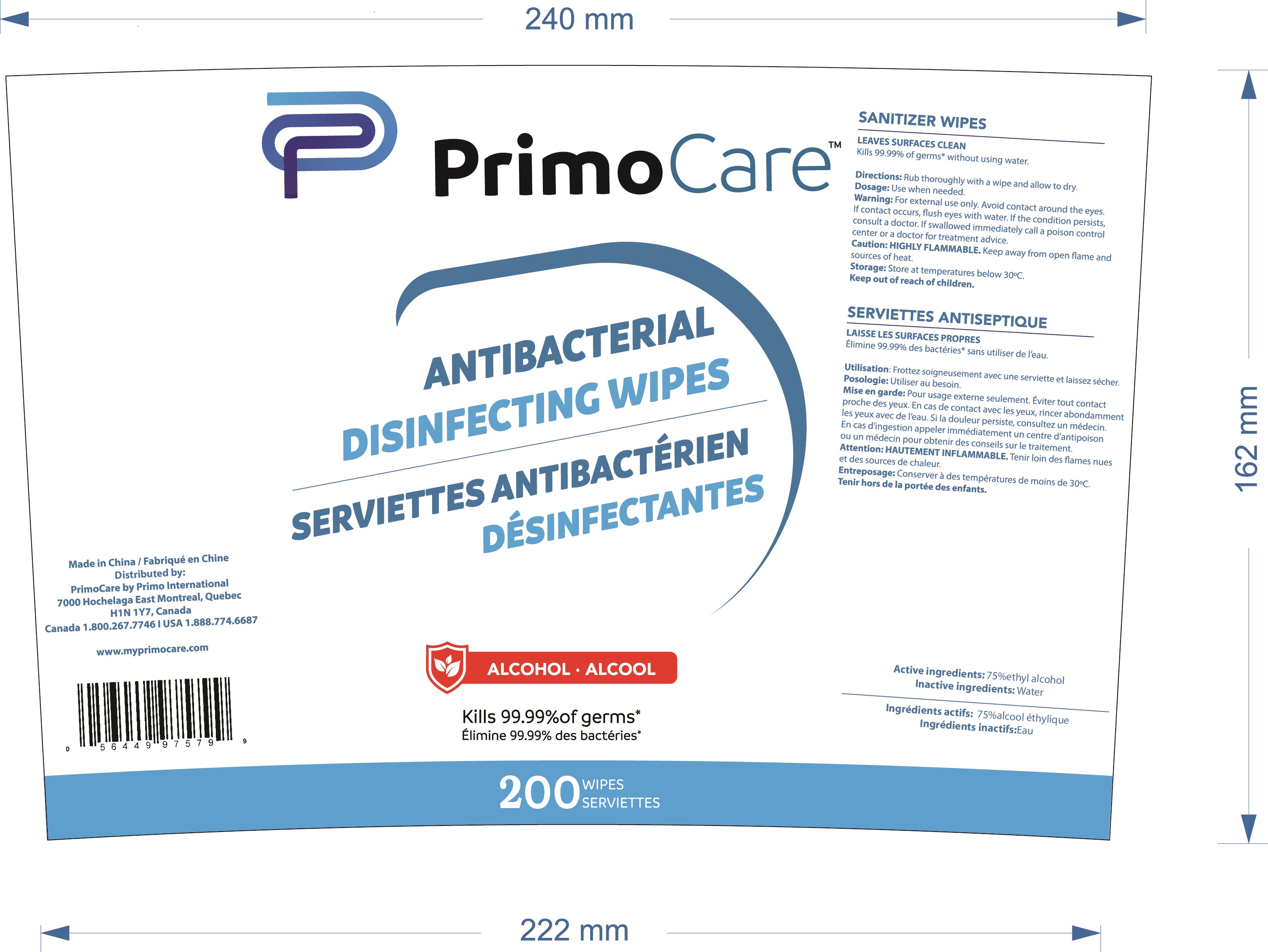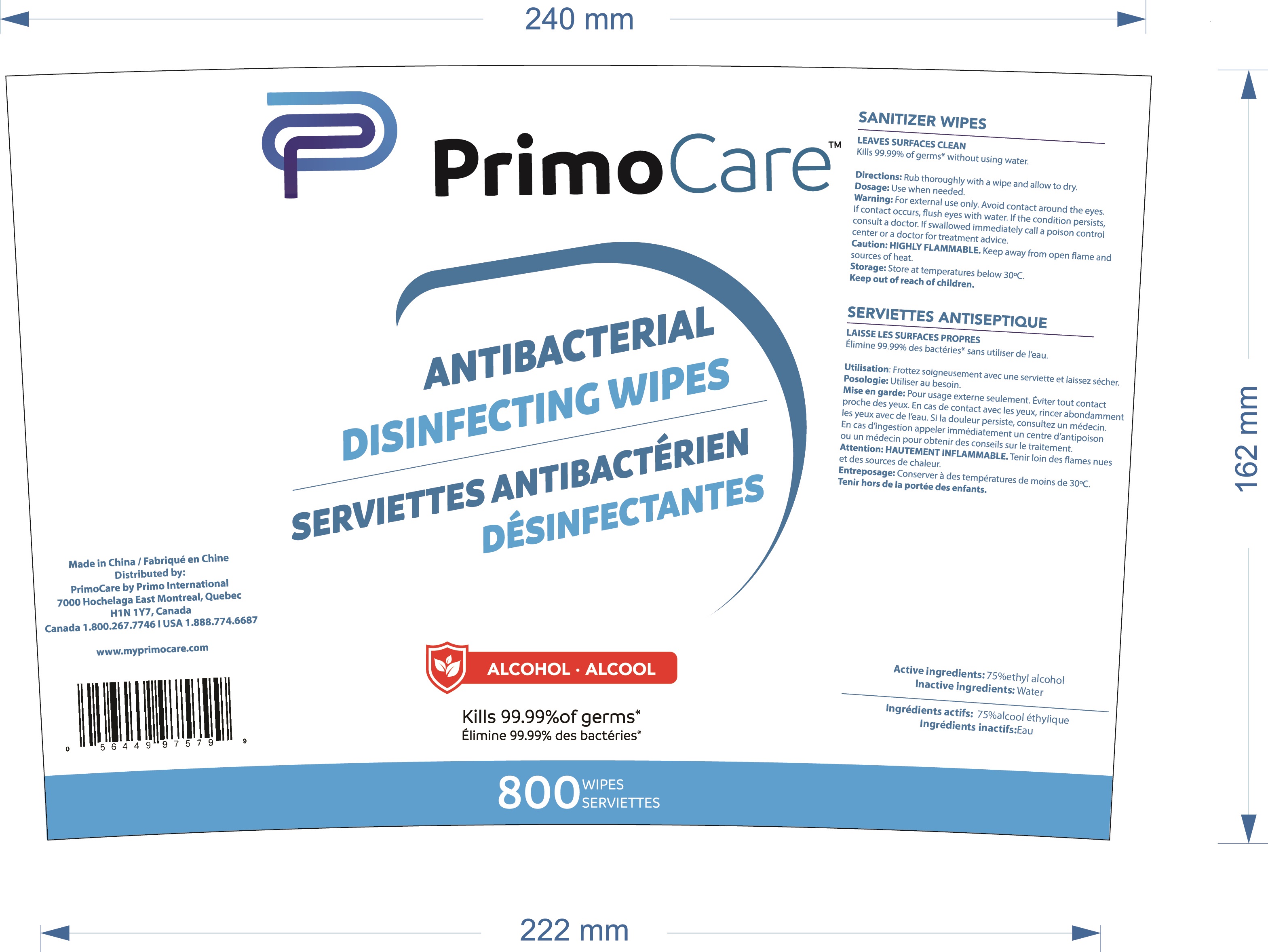 DRUG LABEL: Sanitizing wipes
NDC: 81390-001 | Form: CLOTH
Manufacturer: Ningbo Longco Commodity Co., LTD
Category: otc | Type: HUMAN OTC DRUG LABEL
Date: 20210119

ACTIVE INGREDIENTS: ALCOHOL 75 mL/100 1
INACTIVE INGREDIENTS: WATER

81390-001
Sanitizing wipes

Active Ingredient(s)

Active ingredients: 75%ethyl alcohol

Purpose

LEAVES SURFACES CLEAN

Use

LEAVES SURFACES CLEAN
Kills 99.99% of germs* without using water.

Warnings

For external use only. Avoid contact around the eyes.
If contact occurs, flush eyes with water.
If the condition persists, consult a doctor If swallowed immediately call a poison control center or a doctor for treatment advice.

Do not use

If contact occurs, flush eyes with water.

WHEN USING

Caution: HIGHLY FLAMMABLE. Keep away from open flame and sources of heat
If contact occurs, flush eyes with water.
If the condition persists, consult a doctor If swallowed immediately call a poison control center or a doctor for treatment advice.

STOP USE

If the condition persists, consult a doctor If swallowed immediately call a poison control center or a doctor for treatment advice.

Keep out of reach of children.Keep out of reach of children.

Directions

Rub thoroughly with a wipe and allow to dry.
Use when needed.

Other information

Storage: Storage: Store at temperatures below 30°C.

Inactive ingredients

Inactive ingredients: Water

Package Label - Principal Display Panel

81390-001-00 3sheets in 1bag

81390-001-01 5sheets in 1bag

81390-001-02 10sheets in 1bag

81390-001-03 20sheets in 1bag

81390-001-04 50sheets in 1bag

81390-001-05 80sheets in 1bag

81390-001-06 80sheets in 1 DRUM

81390-001-07 100sheets in 1 DRUM

81390-001-08 200sheets in 1 DRUM

81390-001-09 800sheets in 1 DRUM